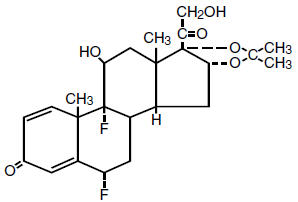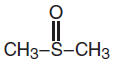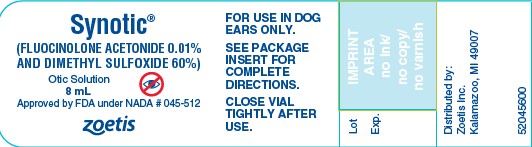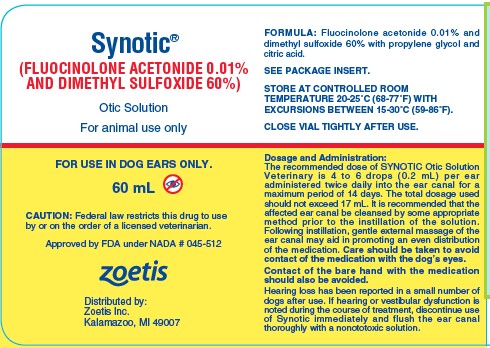 DRUG LABEL: Synotic Otic
NDC: 54771-0120 | Form: SOLUTION
Manufacturer: Zoetis Inc.
Category: animal | Type: PRESCRIPTION ANIMAL DRUG LABEL
Date: 20250523

ACTIVE INGREDIENTS: FLUOCINOLONE ACETONIDE 0.1 mg/1 mL; DIMETHYL SULFOXIDE 600 mg/1 mL
INACTIVE INGREDIENTS: PROPYLENE GLYCOL; CITRIC ACID MONOHYDRATE

Synotic® Otic Solution

Synotic®

(FLUOCINOLONE ACETONIDE 0.01% AND DIMETHYL SULFOXIDE 60%)

Otic Solution

For animal use only

CAUTION

Federal law restricts this drug to use by or on the order of a licensed veterinarian.

FORMULATION

Each mL of the solution contains 0.01% fluocinolone acetonide (6α, 9α-difluoro-11β,16α,17,21-tetrahydroxypregna- 1,4-diene-3,20-dione, cyclic 16, 17-acetal with acetone) and 60% dimethyl sulfoxide in propylene glycol and citric acid.

GENERAL

Fluocinolone acetonide is an odorless crystalline powder essentially white in color. Other physical characteristics include:

Melting point | 265°–277°C.
Molecular weight | 452.50

The structural formulation is:

Dimethyl sulfoxide (DMSO) an oxidation product of dimethyl sulfide, is the lowest member of the group of alkyl sulfoxides with a general formula of RSOR. Its structural formula is:

It mixes freely with water with the evolution of heat and lowers the freezing point of aqueous solutions. It is soluble in many other compounds including ethanol, acetone, diethyl ether, glycerin, toluene, benzene and chloroform. DMSO is a solvent for many aromatic and unsaturated hydrocarbons as well as inorganic salts and nitrogen-containing compounds. DMSO has a high dielectric constant due to the polarity of the sulfur-oxygen bond. Its basicity is slightly greater than water due to enhanced electron density at the oxygen atom. It forms crystalline salts with strong protic acids and coordinates with Lewis acids. It modifies hydrogen bonding.

Propylene glycol is well established as being nonsensitizing, nontoxic and has antimicrobial activity. It has been selected for this formulation because of several useful properties: There is a low surface tension permitting great spreadability and penetration; its drying properties make it valuable in moist areas; the corticosteroid is highly soluble and stable in this vehicle; and a relatively slow rate of evaporation maintains the solution state for an adequate time to allow distribution and contact with all parts of the ear.

INDICATIONS

SYNOTIC Otic Solution Veterinary is indicated for the relief of pruritus and inflammation associated with acute and chronic otitis in the dog.

DOSAGE AND ADMINISTRATION

The recommended dose of SYNOTIC Otic Solution Veterinary is 4 to 6 drops (0.2 mL) per ear administered twice daily into the ear canal for a maximum period of 14 days. The total dosage used should not exceed 17 mL. It is recommended that the affected ear canal be cleansed by some appropriate method prior to the instillation of the solution. Following instillation, gentle external massage of the ear canal may aid in promoting an even distribution of the medication. Care should be taken to avoid contact of the medication with the dog’s eyes.
Contact of the bare hand with the medication should also be avoided.
Hearing loss has been reported in a small number of dogs after use. If hearing or vestibular dysfunction is noted during the course of treatment, discontinue use of Synotic immediately and flush the ear canal thoroughly with a nonototoxic solution.

WARNING

Clinical and experimental data have demonstrated that corticosteroids administered orally or by injection to animals may induce the first stage of parturition if used during the last trimester of pregnancy and may precipitate premature parturition followed by dystocia, fetal death, retained placenta, and metritis.

Additionally, corticosteroids administered to dogs, rabbits, and rodents during pregnancy have resulted in cleft palate in offspring. Corticosteroids administered to dogs during pregnancy have also resulted in other congenital anomalies, including deformed forelegs, phocomelia and anasarca.

.

PRECAUTIONS

There should be careful initial evaluation and follow-up of infected ears. Incomplete response or exacerbation of corticosteroid responsive lesions may be due to the presence of an infection which requires identification or antibiotic sensitivity testing, and the use of the appropriate antimicrobial agent. As with any corticosteroid, animals with a generalized infection should not be treated with this product without proper supportive antimicrobial therapy. Preparations with DMSO should not be used in pregnant animals since studies in chick embryos and guinea pigs have indicated it is teratogenic and embryotoxic.

SYNOTIC (fluocinolone acetonide and dimethyl sulfoxide) Otic Solution Veterinary is recommended for topical application to the ear canal of the dog only.

DO NOT ADMINISTER BY ANY OTHER ROUTE.

SIDE EFFECTS

A transient, but mild, stinging sensation may be experienced by some animals when the solution is applied to denuded areas. The effect will disappear as healing progresses. A temporary increase in temperature of the area may also be noted.

Corticosteroid therapy will generally cause a remission of signs of allergic origin. However, until the causative agent is identified and removed from the animal’s environment, the condition may recur when therapy is terminated.

Ordinarily, side effects are not encountered with topically applied corticosteroids; but as with all drugs, some animals may exhibit unfavorable local and/or systemic reactions. A local reaction may be due to sensitization to the corticosteroid or one of the other components of the solution.

It is known that DMSO enhances the percutaneous absorption of topically applied corticosteroids and the veterinarian should be aware of possible systemic reactions in this situation. Accordingly, this product is contraindicated wherever systemic corticosteroids would be dangerous. Adrenal suppression, weight loss and increased susceptibility to infections may be evidenced with the use of this drug, especially in overdosage. Therefore, care should be taken to assure that the recommended dosage is not exceeded.

In the presence of local and/or systemic side effects, the drug should be withdrawn. When a local reaction occurs other therapeutic measures should be instituted. Therapy can usually be resumed at a lower dose once systemic signs abate, without further recurrence of the problem.

Absorption of DMSO following topical application may result in an odorous breath described as oyster or garlic-like with an unpleasant taste. Some animals and clients may find this objectionable but these effects are transient and not considered to be of serious consequence.

PHARMACOLOGY

Fluocinolone acetonide is chemically related to prednisolone and possesses marked anti-inflammatory properties when applied topically. It has been shown to have over 100 times the anti-inflammatory activity of hydrocortisone. Fluocinolone acetonide decreases edema, inflammation, erythema, infiltration and pruritus with its associated scratching and excoriation. Following topical application of fluocinolone acetonide, especially at elevated dosage levels, systemic effects such as some adrenal suppression and weight loss have been observed. These effects, however, have been demonstrated to be reversible.

It has been demonstrated in the human, by both in vivo and in vitro methods, that DMSO enhances the percutaneous absorption of various compounds including steroids, vasoconstrictors, antiperspirants and dyes, as well as an anthelmintic (thiabendazole) and a skin antiseptic (hexachlorophene) (1,2,3,4,5). It was also shown in immature female rats that both estrogens and corticoids applied topically in DMSO exerted some of their usual biological effects (6,7).

TOXICOLOGY

Dimethyl Sulfoxide

Changes in the refractive index of the lens of the eye and nuclear cataracts have been observed in animals with the oral use of DMSO and appeared to be related to high daily doses or a long duration of daily therapy. The lens changes were first observed in dogs receiving 5 g/kg of DMSO orally daily after 9 weeks of administration. Later studies revealed ocular effects at 4.5 mL/kg in 5–9 weeks and at 0.5–1/mL/kg for 19 weeks. These eye changes were slowly reversible but with a definite species difference, the dog being the slowest to exhibit improvement.

In a subsequent study conducted in dogs to determine the effects of a 90% dimethyl sulfoxide solution applied topically at a total daily dose of 20–60 mL for 21 consecutive days, no clinically meaningful ophthalmological effects were noted. No significant variations were observed in hematologic values or in other blood measurements including glucose, BUN, SGOT and plasma electrophoresis.

DMSO may facilitate the systemic absorption of other topically-applied drugs and may have a potentiating effect on drugs administered systemically. Medications containing DMSO as a vehicle should be used judiciously when administered in conjunction with other pharmaceutical preparations especially those affecting the cardiovascular and central nervous systems. Other medication should not be present at the site of its topical application. If other topical medications are indicated they should not beapplied until after the medication containing DMSO is thoroughly dry.

DMSO is a potent solvent and may have a deleterious effect upon fabrics, plastics and other materials. Care should be taken to prevent physical contact with SYNOTIC (fluocinolone acetonide and dimethyl sulfoxide) Otic Solution Veterinary when the drug is applied. Contact with the treated area should be avoided until drying of the treated ear canal has occurred.

Fluocinolone Acetonide

It is estimated that the maximum dosage dogs will tolerate, when fed fluocinolone acetonide daily for a period of 2 weeks, is less than 0.125 mg/kg. At this dose level animals lost weight and displayed diarrhea and intestinal inflammation. When dogs were fed fluocinolone acetonide daily for a period of three months the maximum daily dose tolerated is estimated to be between 0.05 and 0.125 mg/kg. At the lower dose the adrenal glands of treated dogs appeared somewhat smaller than the controls.

The intravenous lethal dose of fluocinolone acetonide in 50% aqueous propylene glycol is in excess of 50 mg/kg in mice and rabbits, in excess of 40 mg/kg in dogs, and in excess of 30 mg/kg in rats. The compound induced no pyrogenic response in rabbits nor sensitizing effects in guinea pigs. Gross or histologic effects were not encountered.

The lethal dose orally in dogs and cats exceeds 1 g/kg. There was lymphocytopenia in all animals and erythrocytosis in cats employed in this study.

Two g/kg of 0.05 to 0.2% fluocinolone acetonide applied daily 5 days per week for 3 weeks to the abraded skin of rabbits, resulted in neither local nor systemic toxicity.

Similar applications to intact skin for 13 weeks, including an additional group at 0.025%, resulted only in decreased body weight and adrenal size.

A small decrease in body weight was seen in dogs treated for 7 days with 0.5 mL (15 drops)/ear/day of SYNOTIC (fluocinolone acetonide and dimethyl sulfoxide) Otic Solution Veterinary. In dogs which were treated for 21 days with 1.5 mL (45 drops)/ear/day of this formulation there was a slight loss of weight with changes in the adrenal glands consistent with corticosteroid treatment. This indicates absorption from the dogs’ ears. This absorption, and concomitant effects, are probably enhanced by the action of DMSO.

In a subsequent study, dogs were treated with the recommended therapeutic dose of SYNOTIC Otic Solution Veterinary at the rate of 12 drops (0.4 mL) per ear daily for 21 consecutive days. No significant changes were detected in clinical chemistry, urinalysis, or hematology. A reversible adrenal cortical atrophy with cortical cytoplasmic vacuolization was noted. An equivocal response was noted following ACTH administration on the day after SYNOTIC Otic Solution Veterinary treatment was suspended, but after a one week recovery period, there was a definite eosinophile depression and recovery following ACTH administration, indicating normal adrenal function.

STORAGE INFORMATION

Store at controlled room temperature 20°-25°C (68°-77°F) with excursions between 15°-30°C (59°-86°F). CAUTION: VERY HYGROSCOPIC. CLOSE VIAL TIGHTLY AFTER USE.

HOW SUPPLIED

SYNOTIC® (fluocinolone acetonide and dimethyl sulfoxide) Otic Solution Veterinary available in dropper vials of 8 mL and 60 mL.

REFERENCES

1. Stoughton, R. B. and Fritsch, W., INFLUENCE OF DIMETHYLSULFOXIDE (DMSO) ON HUMAN PERCUTANEOUS ABSORPTION 1964 Arch. Derm. 90, 512–517 Nov. 1964.

2. Stoughton, R. B., HEXACHLOROPHENE DEPOSITION IN HUMAN STRATUM CORNEUM. ENHANCEMENT BY DIMETHYLACETAMIDE, DIMETHYLSULFOXIDE, AND METHYLETHYLETHER 1966 Arch. Derm. 94, 646–648 Nov. 1966.

3. Katz, R. and Hood, R. W., TOPICAL THIABENDAZOLE FOR CREEPING ERUPTION 1966 Arch. Derm. 94, 643–645 Nov. 1966.

4. Sperber, P. A., TREATMENT OF CREEPING ERUPTION WITH ORALLY AND TOPICALLY ADMINISTERED THIABENDAZOLE 1967 J. Fla. M. A., 1059–61 Nov. 1967.

5. Sulzberger, M. B., Cortese, T. A., Fishman, L., Wiley, H. S. and Peyakovich, P. S., SOME EFFECTS OF DMSO ON HUMAN SKIN IN VIVO 1967 Ann. N. Y. Acad. Sci. 141, 437–450 March 1967.

6. Smith, Q. T. and Allison, D. J., UTEROTROPHIC EFFECT OF TOPICALLY APPLIED ESTRADIOL-17β BENZOATE 1967 Acta Derm-Venereol 47, 435-439.

7. Tjan, I. D. and Gunberg, D. L., PERCUTANEOUS ABSORPTION OF TWO STEROIDS DISSOLVED IN DIMETHYL SULFOXIDE IN THE IMMATURE FEMALE RAT 1967 N. Y. Acad. Sci. 141, 406–413 Mar. 1967.

Approved by FDA under NADA # 045-512
zoetis
Distributed by:
Zoetis Inc.
Kalamazoo, MI 49007
Revised: August 2024
52045800

PRINCIPAL DISPLAY PANEL - 8 mL Vial Label

52045600

PRINCIPAL DISPLAY PANEL - 60 mL Vial Label

52189600